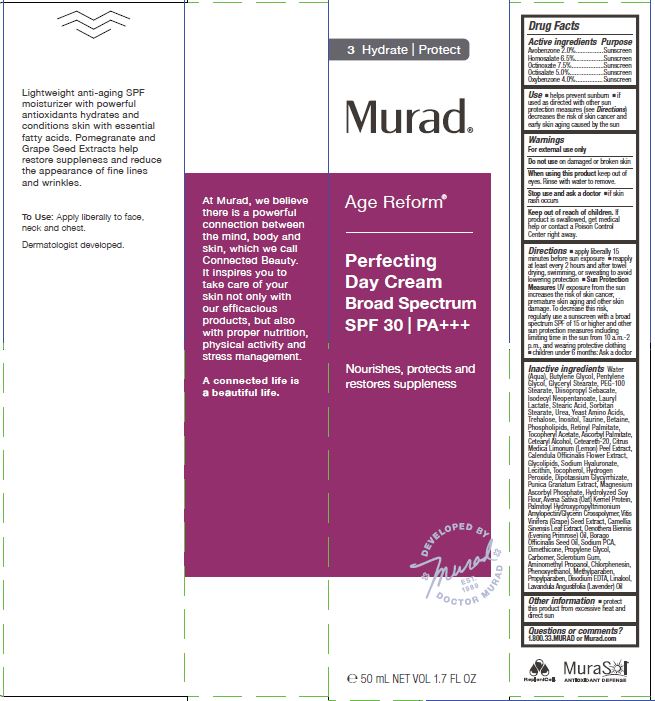 DRUG LABEL: MURAD - AGE REFORM - PERFECTING DAY 
NDC: 70381-104 | Form: CREAM
Manufacturer: Murad, LLC
Category: otc | Type: HUMAN OTC DRUG LABEL
Date: 20201227

ACTIVE INGREDIENTS: AVOBENZONE 2 g/100 mL; HOMOSALATE 6.5 g/100 mL; OCTINOXATE 7.5 g/100 mL; OCTISALATE 5 g/100 mL; OXYBENZONE 4 g/100 mL
INACTIVE INGREDIENTS: WATER; BUTYLENE GLYCOL; PENTYLENE GLYCOL; GLYCERYL MONOSTEARATE; PEG-100 STEARATE; DIISOPROPYL SEBACATE; ISODECYL NEOPENTANOATE; LAURYL LACTATE; STEARIC ACID; SORBITAN MONOSTEARATE; UREA; AMINO ACIDS, SOURCE UNSPECIFIED; TREHALOSE; INOSITOL; TAURINE; BETAINE; OMEGA-3 FATTY ACIDS; VITAMIN A PALMITATE; .ALPHA.-TOCOPHEROL ACETATE; ASCORBYL PALMITATE; CETOSTEARYL ALCOHOL; POLYOXYL 20 CETOSTEARYL ETHER; LEMON PEEL; CALENDULA OFFICINALIS FLOWER; GLYCOL OLEATE; HYALURONATE SODIUM; LECITHIN, SUNFLOWER; TOCOPHEROL; HYDROGEN PEROXIDE; GLYCYRRHIZINATE DIPOTASSIUM; PUNICA GRANATUM WHOLE; MAGNESIUM ASCORBYL PHOSPHATE; SOYBEAN; OAT; PALMITOYL GLYCINE; GRAPE; GREEN TEA LEAF; EVENING PRIMROSE OIL; BORAGE SEED OIL; SODIUM PYRROLIDONE CARBOXYLATE; DIMETHICONE; PROPYLENE GLYCOL; CARBOMER HOMOPOLYMER, UNSPECIFIED TYPE; BETASIZOFIRAN; AMINOMETHYLPROPANOL; CHLORPHENESIN; PHENOXYETHANOL; METHYLPARABEN; PROPYLPARABEN; EDETATE DISODIUM; LINALOOL, (+)-; LAVENDER OIL

MURAD - AGE REFORM - PERFECTING DAY CREAM, BROAD SPECTRUM SPF 30

ACTIVE INGREDIENTS

Avobenzone 2.0%
Homosalate 6.5%
Octinoxate 7.5%
Octisalate 5.0%
Oxybenzone 4.0%

PURPOSE

SUNSCREEN

USES

- helps prevent sunburn
- if used as directed with other sun protection measures (see Directions) decreases the risk of skin cancer and early skin aging caused by the sun.

WARNINGS

For external use only

Do not use on damaged or broken skin

When using this product keep out of eyes. Rinse with water to remove.

Stop use and ask a doctor

- if skin rash occurs

Keep out of reach of children. If product is swallowed, get medical help or contact a Poison Control Center right away.

DIRECTIONS

- apply liberally 15 minutes before sun exposure
- use a water resistant sunscreen if swimming or sweating
- reapply at least every 2 hours
- Sun Protection Measures.pending time in the sun increases your risk of skin cancer and early skin aging. To decrease this risk, regularly use a sunscreen with a Broad Spectrum SPF value of 15 or higher and other sun protection measures including:
- limit time in the sun, especially from 10 a.m. - 2 p.m.
- wear long-sleeved shirts, pants, hats, and sunglasses.
- children under 6 months of age: ask a doctor

INACTIVE INGREDIENTS

Water (Aqua), Butylene Glycol, Pentylene Glycol, Glyceryl Stearate, PEG-100 Stearate, Diisopropyl Sebacate, Isodecyl Neopentanoate, Lauryl
Lactate, Stearic Acid, Sorbitan Stearate, Urea, Yeast Amino Acids, Trehalose, Inositol, Taurine, Betaine, Phospholipids, Retinyl Palmitate,
Tocopheryl Acetate, Ascorbyl Palmitate, Cetearyl Alcohol, Ceteareth-20, Citrus Medica Limonum (Lemon) Peel Extract, Calendula Officinalis Flower Extract, Glycolipids, Sodium Hyaluronate, Lecithin, Tocopherol, Hydrogen Peroxide, Dipotassium Glycyrrhizate, Punica Granatum Extract, Magnesium Ascorbyl Phosphate, Hydrolyzed Soy Flour, Avena Sativa (Oat) Kernel Protein, Palmitoyl Hydroxypropyltrimonium Amylopectin/Glycerin Crosspolymer, Vitis Vinifera (Grape) Seed Extract, Camellia Sinensis Leaf Extract, Oenothera Biennis (Evening Primrose) Oil, Borago Officinalis Seed Oil, Sodium PCA, Dimethicone, Propylene Glycol, Carbomer, Sclerotium Gum, Aminomethyl Propanol, Chlorphenesin, Phenoxyethanol, Methylparaben, Propylparaben, Disodium EDTA, Linalool, Lavandula Angustifolia (Lavender) Oil

OTHER INFORMATION

- protect this product from excessive heat and direct sun

QUESTIONS OR COMMENTS?

1.800.33.MURAD or Murad.com